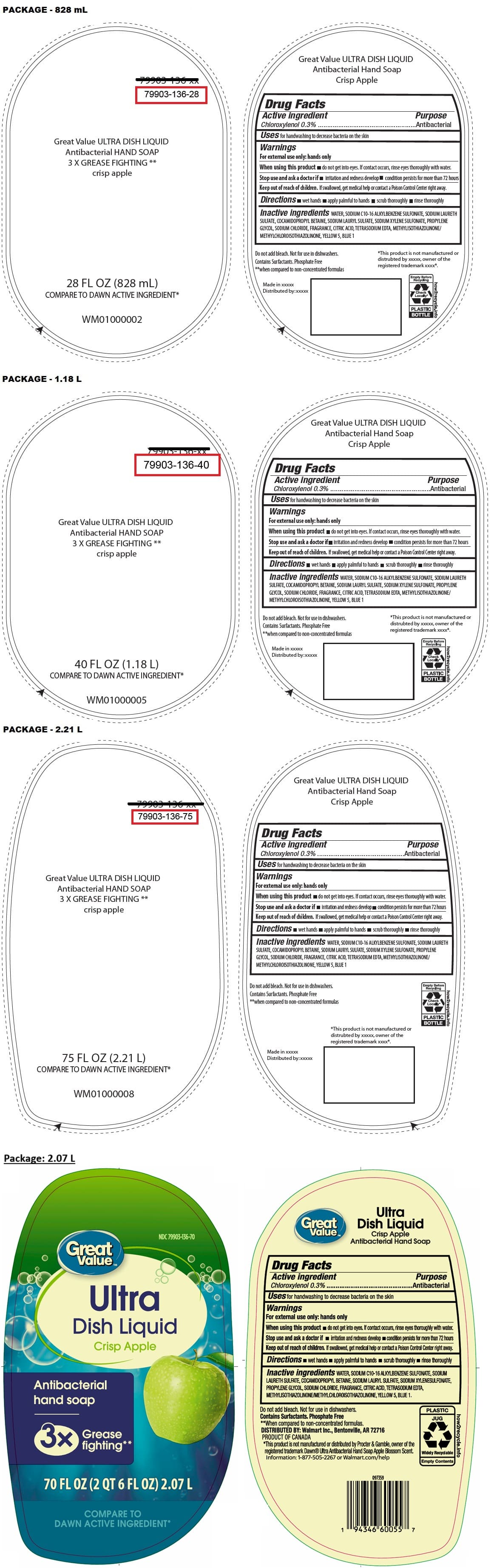 DRUG LABEL: Great Value ULTRA DISH Liquid Antibacterial HANDSOAP crisp apple
NDC: 79903-136 | Form: LIQUID
Manufacturer: WALMART INC.
Category: otc | Type: HUMAN OTC DRUG LABEL
Date: 20260129

ACTIVE INGREDIENTS: CHLOROXYLENOL 0.3 g/100 mL
INACTIVE INGREDIENTS: WATER; DODECYLBENZENESULFONIC ACID; SODIUM LAURETH-2 SULFATE; COCAMIDOPROPYL BETAINE; SODIUM LAURYL SULFATE; SODIUM XYLENESULFONATE; PROPYLENE GLYCOL; SODIUM CHLORIDE; ANHYDROUS CITRIC ACID; EDETATE SODIUM; METHYLCHLOROISOTHIAZOLINONE/METHYLISOTHIAZOLINONE MIXTURE; FD&C YELLOW NO. 5; FD&C BLUE NO. 1

Great ValueTM Ultra Dish Liquid Antibacterial hand soap

Active ingredient

Chloroxylenol 0.3%

Purpose

Antibacterial

Uses

for handwashing to decrease bacteria on the skin

Warnings

For external use only: hands only

When using this product • do not get into eyes. If contact occurs, rinse eyes thoroughly with water.

Stop use and ask a doctor if • irritation and redness develop • condition persists for more than 72 hours

Keep out of reach of children. If swallowed, get medical help or contact a Poison Control Center right away.

Directions

• wet hands • apply palmful to hands • scrub thoroughly • rinse thoroughly

Inactive ingredients

WATER, SODIUM C10-16 ALKYLBENZENE SULFONATE, SODIUM LAURETH SULFATE, COCAMIDOPROPYL BETAINE, SODIUM LAURYL SULFATE, SODIUM XYLENESULFONATE, PROPYLENE GLYCOL, SODIUM CHLORIDE, FRAGRANCE, CITRIC ACID, TETRASODIUM EDTA, METHYLISOTHIAZOLINONE/METHYLCHLOROISOTHIAZOLINONE, YELLOW 5, BLUE 1.

3X Grease fighting**

COMPARE TO DAWN ACTIVE INGREDIENT*

Do not add bleach. Not for use in dishwashers.

Contains Surfactants. Phosphate Free
**when compared to non-concentrated formulas.

DISTRIBUTED BY: Walmart Inc., Bentonville, AR 72716

PRODUCT OF CANADA
'This product is not manufactured or distributed by Procter & Gamble, owner of the registered trademark Dawn® Ultra Antibacterial Hand Soap Apple Blossom Scent.

Information: 1-877-505-2267 or Walmart.com/help